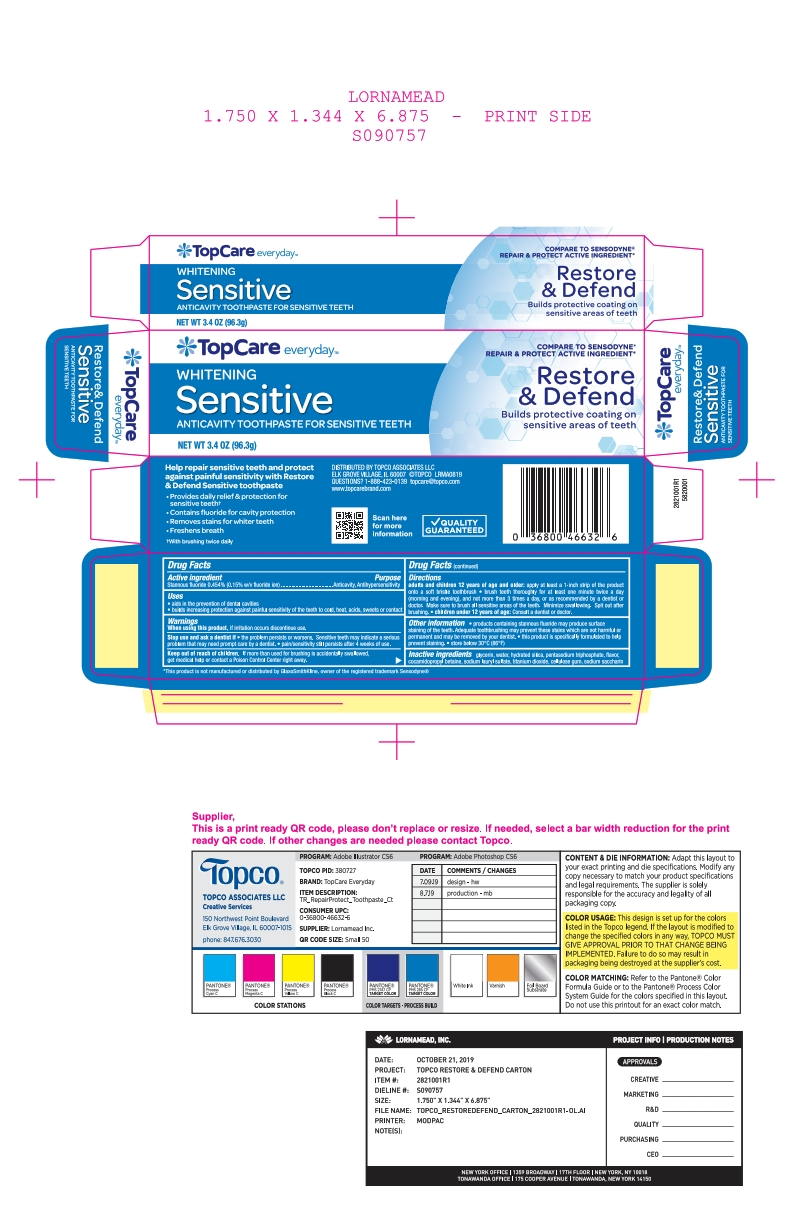 DRUG LABEL: Sensitive Whitening Anticavity
NDC: 36800-201 | Form: PASTE, DENTIFRICE
Manufacturer: Topco
Category: otc | Type: HUMAN OTC DRUG LABEL
Date: 20251113

ACTIVE INGREDIENTS: STANNOUS FLUORIDE 0.15 g/100 g
INACTIVE INGREDIENTS: SACCHARIN SODIUM; WATER; TITANIUM DIOXIDE; CARBOXYMETHYLCELLULOSE SODIUM, UNSPECIFIED FORM; COCAMIDOPROPYL BETAINE; SODIUM LAURYL SULFATE; HYDRATED SILICA; SODIUM TRIPOLYPHOSPHATE ANHYDROUS; GLYCERIN

5820001 Topco Restore & Defend

Active Ingredient Purpose

Stannous fluoride 0.454% (0.15% w/v fluoride ion) .......................... Anticavity/Antihypersensitivity

INDICATIONS AND USAGE

Uses

- aids in the prevention of dental cavities
- builds increasing protection against painful sensitivity of the teeth to cold, heat, acids, sweets or contact

When using this product, if irritation occurs discontinue use

Stop use and ask a dentist if

- the problem persists or worsens. Sensitive teeth may indicate a serious problem that may need prompt care by a dentist
- pain/sensitivity still persists after 4 weeks of use

Keep out of reach of children. If more than used for brushing is accidentally swallowed, get medical help or contact a Poison Control Center right away.

Directions

adults and children 12 years of age and older: apply at least a 1-inch strip of the product onto a soft bristle toothbrush

- brush teeth thoroughly for at least one minute twise a day (morning and evening), and not more than 3 times a day, or as recommended by a dentist or doctor. Make sure to brush all sensitive areas of the teeth. Minimize swallowing. Spit out after brushing.
- children under 12 years of age: Consult a dentist or doctor.

Other information

products containing stannous fluoride may produce surface staining of the teeth. Adequate toothbrushing may prevent these stains which are not harmful or permanent and may be removed by your dentist

this product is specifically formulated to prevent staining

store below 30°C (86°F)

INACTIVE INGREDIENT

glycerin, water, hydrated silica, pentasodium triphosphate, flavor, cocamidopropyl betaine, sodium lauryl sulfate, titanium dioxide, cellulose gum, sodium saccharin

PACKAGE LABEL

Whitening

Sensitive

Anticavity Toothpaste for Sensitive Teeth

Net Wt 3.4 oz (96.3g)

Compare to Sensodyne

Repair & Protect Active Ingredient*

Restore

& Defend

Builds protective coating on

sensitive areas of teeth